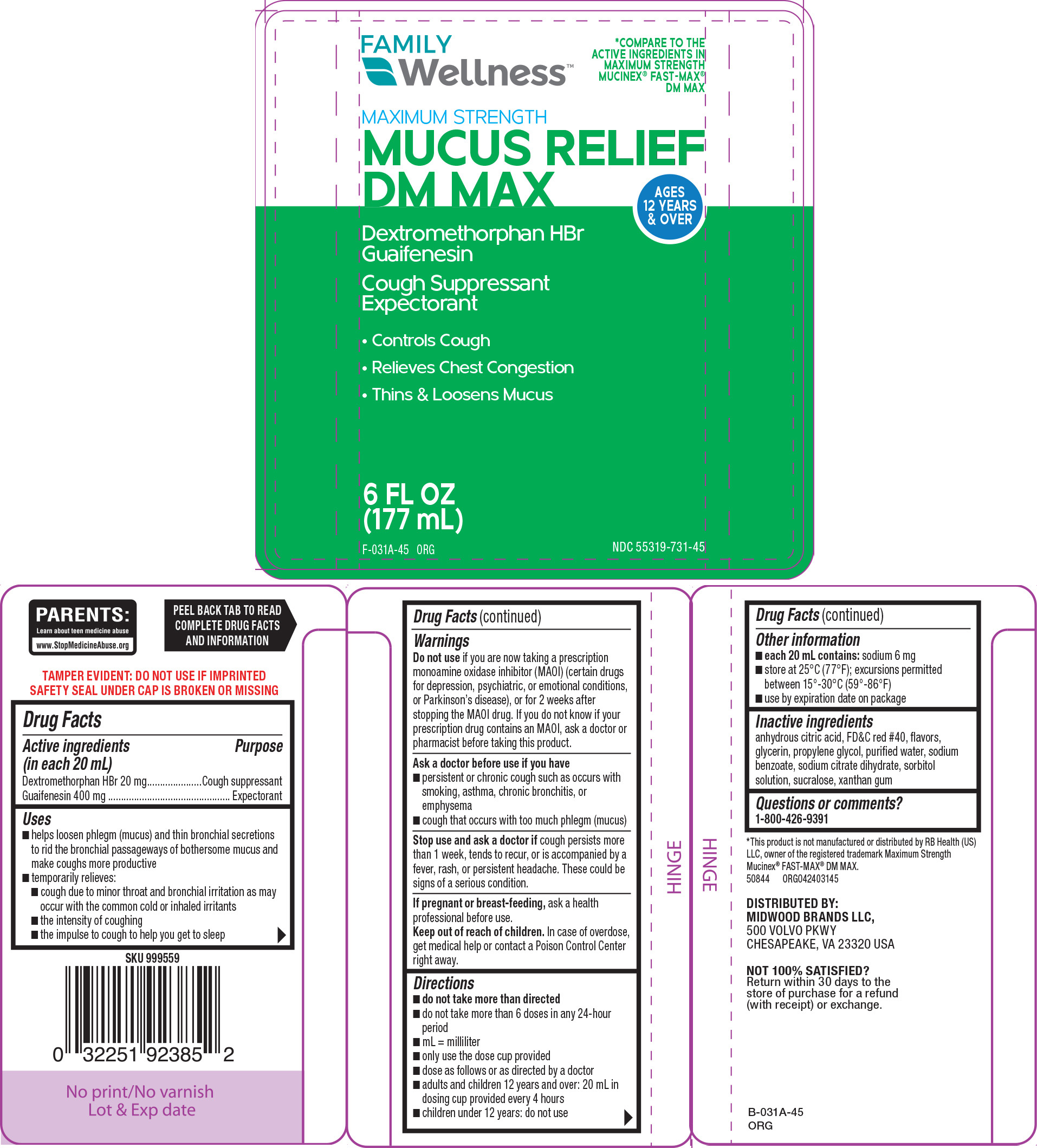 DRUG LABEL: Mucus Relief DM Max
NDC: 55319-731 | Form: SOLUTION
Manufacturer: Family Dollar Services Inc
Category: otc | Type: HUMAN OTC DRUG LABEL
Date: 20260120

ACTIVE INGREDIENTS: DEXTROMETHORPHAN HYDROBROMIDE 20 mg/20 mL; GUAIFENESIN 400 mg/20 mL
INACTIVE INGREDIENTS: ANHYDROUS CITRIC ACID; FD&C RED NO. 40; GLYCERIN; PROPYLENE GLYCOL; WATER; SODIUM BENZOATE; TRISODIUM CITRATE DIHYDRATE; SORBITOL SOLUTION; SUCRALOSE; XANTHAN GUM

Family Wellness 44-031A

Active ingredients (in each 20 mL)

Dextromethorphan HBr 20 mg
Guaifenesin 400 mg

Purpose

Cough suppressant
Expectorant

Uses

- helps loosen phlegm (mucus) and thin bronchial secretions to rid the bronchial passageways of bothersome mucus and make coughs more productive
- temporarily relieves:
  - cough due to minor throat and bronchial irritation as may occur with the common cold or inhaled irritants
  - the intensity of coughing
  - the impulse to cough to help you get to sleep

Warnings

Do not use

if you are now taking a prescription monoamine oxidase inhibitor (MAOI) (certain drugs for depression, psychiatric, or emotional conditions, or Parkinson’s disease), or for 2 weeks after stopping the MAOI drug. If you do not know if your prescription drug contains an MAOI, ask a doctor or pharmacist before taking this product.

Ask a doctor before use if you have

- persistent or chronic cough such as occurs with smoking, asthma, chronic bronchitis, or emphysema
- cough that occurs with too much phlegm (mucus)

Stop use and ask a doctor if

cough persists more than 1 week, tends to recur, or is accompanied by a fever, rash, or persistent headache. These could be signs of a serious condition.

If pregnant or breast-feeding,

ask a health professional before use.

Keep out of reach of children.

In case of overdose, get medical help or contact a Poison Control Center right away.

Directions

- do not take more than directed
- do not take more than 6 doses in any 24-hour period
- mL = milliliter
- only use the dose cup provided
- dose as follows or as directed by a doctor
- adults and children 12 years and over: 20 mL in dosing cup provided every 4 hours
- children under 12 years: do not use

Other information

- each 20 mL contains: sodium 6 mg
- use by expiration date on package
- store at 25°C (77°F); excursions permitted between 15°-30°C (59°-86°F)

Inactive ingredients

anhydrous citric acid, FD&C red #40, flavors, glycerin, propylene glycol, purified water, sodium benzoate, sodium citrate dihydrate, sorbitol solution, sucralose, xanthan gum

Questions or comments?

1-800-426-9391

Principal display panel

FAMILY
Wellness™

*COMPARE TO THE
ACTIVE INGREDIENTS IN
MAXIMUM STRENGTH
MUCINEX® FAST-MAX®
DM MAX

MAXIMUM STRENGTH
MUCUS RELIEF
DM MAX

Dextromethorphan HBr
Guaifenesin

Cough Suppressant
Expectorant

• Controls Cough
• Relieves Chest Congestion
• Thins & Loosens Mucus

AGES
12 YEARS
& OVER

6 FL OZ
(177 mL)

NDC 55319-731-45

TAMPER EVIDENT: DO NOT USE IF IMPRINTED
SAFETY SEAL UNDER CAP IS BROKEN OR MISSING

PARENTS:
Learn about teen medicine abuse
www.StopMedicineAbuse.org

*This product is not manufactured or distributed by RB Health (US)
LLC, owner of the registered trademark Maximum Strength
Mucinex® FAST-MAX® DM MAX.
50844 ORG042403145

DISTRIBUTED BY:
MIDWOOD BRANDS LLC,
500 VOLVO PKWY
CHESAPEAKE, VA 23320 USA

NOT 100% SATISFIED?
Return within 30 days to the
store of purchase for a refund
(with receipt) or exchange.

Family Wellness 44-031A